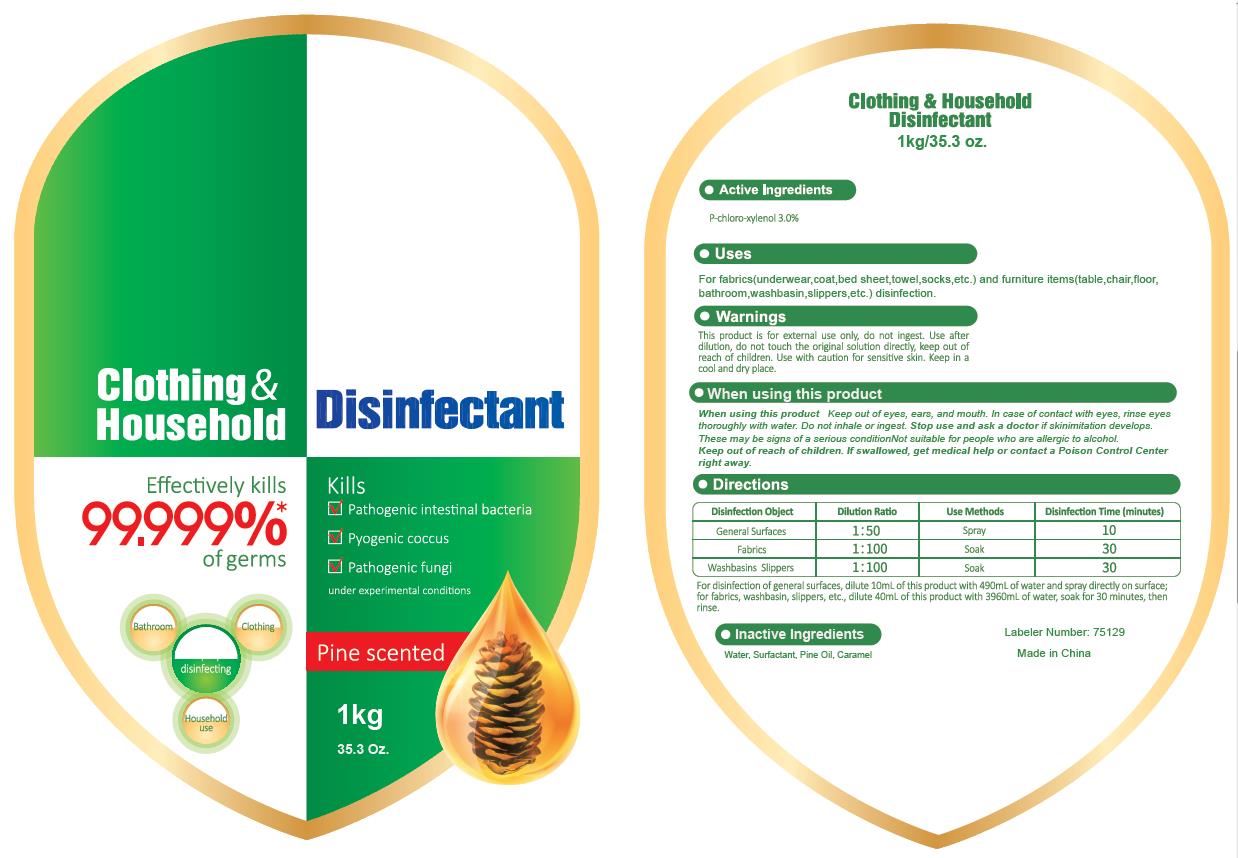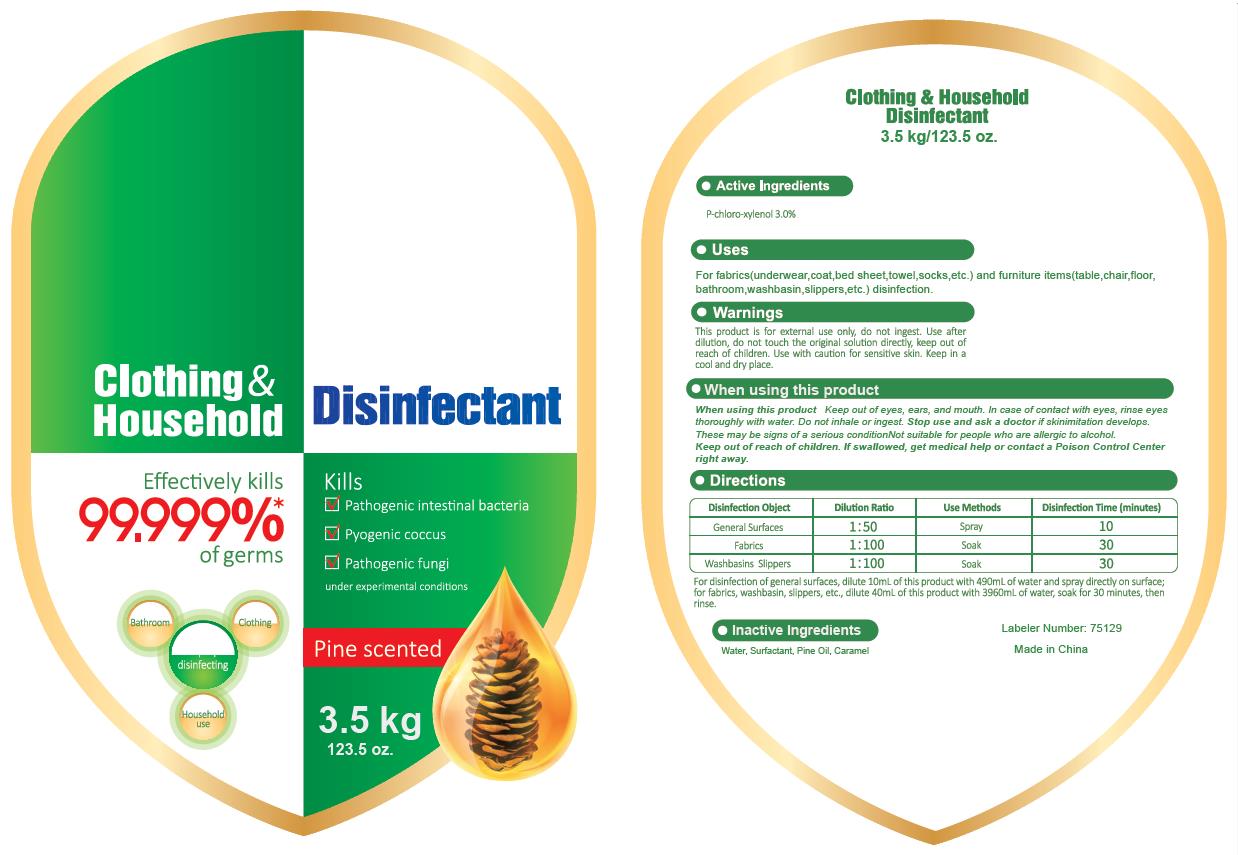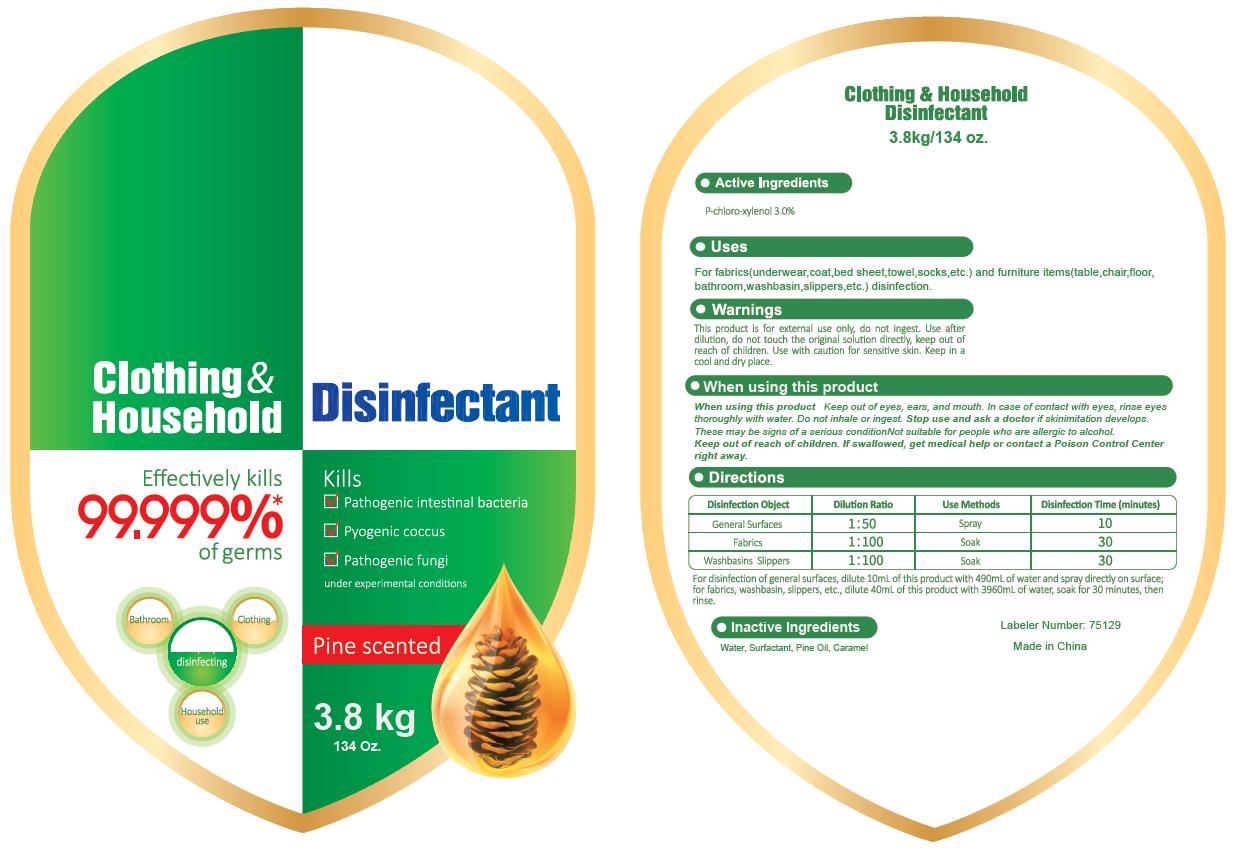 DRUG LABEL: Clothing and Household Disinfectant
NDC: 75129-003 | Form: LIQUID
Manufacturer: Shanghai Rayshine ENVI-TECH Developing CO., Ltd.
Category: otc | Type: HUMAN OTC DRUG LABEL
Date: 20200611

ACTIVE INGREDIENTS: CHLOROXYLENOL 3 kg/100 kg
INACTIVE INGREDIENTS: WATER; BERACTANT; WHITE PINE OIL; CARAMEL

Clothing & Household Disinfectant

Active Ingredient

P-chloro-xvlenol 3.0%

Purpose

/

Uses

For fabrics(underwear, coat, bed sheet, towel, socks, etc.) and furniture items(table, chair, floor, bathroom, washbasin, slippers, etc.) disinfection

Do not use

/

When using this product Keep out of eyes, ears, and mouth. In case of contact with eyes, rinse eyes thoroughly with water.
Do not inhale or ingest.

Stop use and ask a doctor if skinimitation develops.
These may be signs of a serious condition Not suitable for people who are allergic to alcohol.

Keep out of reach of children. If swallowed, get medical help or contact a Poison Control Center right away.

Directions

For disinfection of general surfaces, dilute 10mL of this product with 490mL of water and spray directly on surface for fabrics, washbasin, slippers, etc. dilute 40mL of this product with 3960mL of water, soak for 30 minutes, then rinse.

Other information

/

Inactive ingredients

Water, Surfactant. Pine oil. Caramel